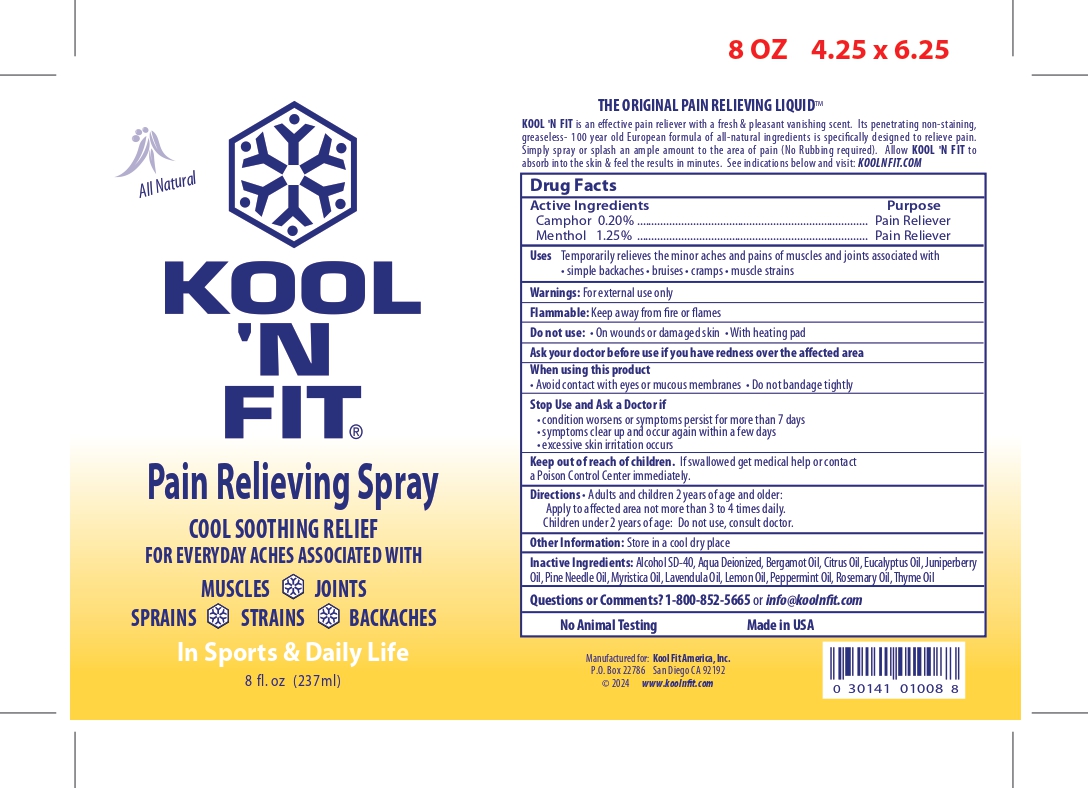 DRUG LABEL: Pain Reliever
NDC: 84733-302 | Form: SPRAY
Manufacturer: Kool 'N Fit Inc.
Category: otc | Type: HUMAN OTC DRUG LABEL
Date: 20251113

ACTIVE INGREDIENTS: CAMPHOR (SYNTHETIC) 0.2 g/100 g; MENTHOL 1.25 g/100 g
INACTIVE INGREDIENTS: WATER; BERGAMOT OIL; POLYSORBATE 20; PEPPERMINT OIL; TERT-BUTYL ALCOHOL; NUTMEG OIL; PINE NEEDLE OIL (PINUS MUGO); THYME OIL; LEMON OIL; ROSEMARY OIL; EUCALYPTUS OIL; JUNIPER BERRY OIL; LAVENDER OIL

CRL (as CMO) Kool N Fit Inc. - Pain Reliever (84733-302)

OTHER INFO

Store in a cool dry place

INACTIVE INGREDIENT

ALCOHOL SDA-40, AQUA DEIONIZED, USP, BERGAMOT OIL, CITRUS OIL, EUCALYPTUS OIL, JUNIPERBERRY OIL, PINE NEEDLE OIL, MYRISTICA OIL, LAVENDULA OIL, LEMON OIL, PEPPERMINT OIL, ROSEMARY OIL, THYME OIL

KEEP OUT OF REACH OF CHILDREN

KEEP OUT OF REACH CHILDREN - IF SWALLOWED GET MEDICAL HELP OR CONTACT A POISON CONTROL CENTER IMMEDIATELY.

DIRECTION

ADULTS AND CHILDREN 2 YEARS OF AGE AND OLDER:

APPLY TO AFFECTED AREA NOT MORE THAN 3 TO 4 TIMES DAILY.

CHILDREN UNDER 2 YEARS OF AGE. DO NOT USE, CONSULT DOCTOR.

WARNING

FOR EXTERNAL USE ONLY.

ACTIVE INGREDIENT

Camphor 0.20%

Menthol 1.25%

PURPOSE

for the temporary relief of minor aches and pains of muscle and joints asscoiated with simple backache, strains, brusies and sprains.

USE

USE ONLY AS DIRECTED.

RECENT MAJOR CHANGES SECTION

COMPLETE ALL CONTENT SECTIONS TO ALIGN WITH PRODUCT PACKAGING

PRODUCT LABEL

KOOL N FIT - PAIN RELIEVING SPRAY